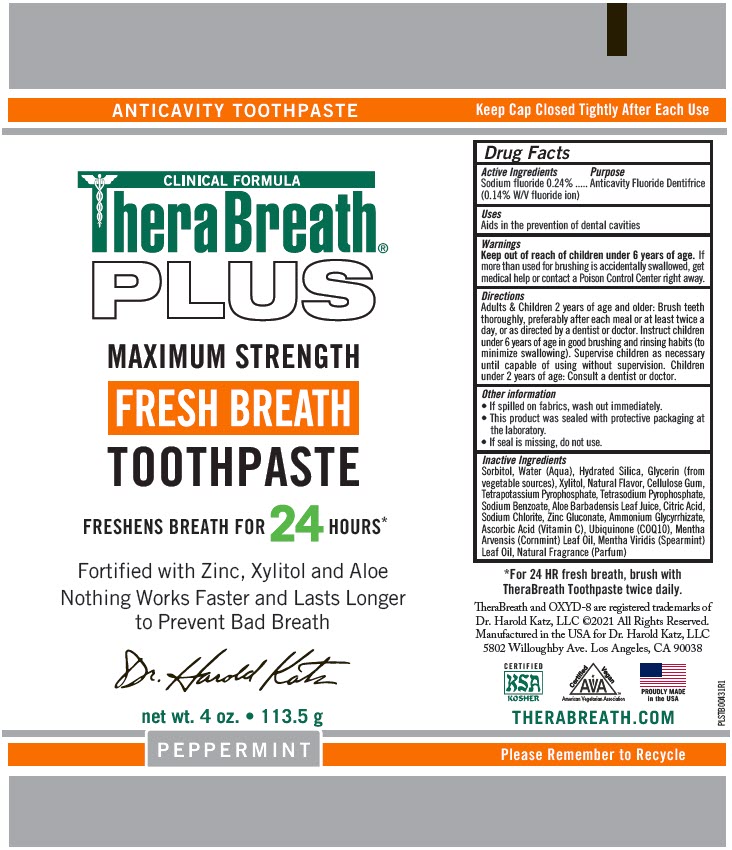 DRUG LABEL: TheraBreath Plus Fresh Breath
NDC: 10237-264 | Form: PASTE, DENTIFRICE
Manufacturer: Church & Dwight Co., Inc.
Category: otc | Type: HUMAN OTC DRUG LABEL
Date: 20251203

ACTIVE INGREDIENTS: SODIUM FLUORIDE 0.24 g/100 g
INACTIVE INGREDIENTS: SORBITOL; HYDRATED SILICA; GLYCERIN; XYLITOL; CARBOXYMETHYLCELLULOSE SODIUM, UNSPECIFIED; POTASSIUM PYROPHOSPHATE; SODIUM PYROPHOSPHATE; SODIUM BENZOATE; ALOE VERA LEAF; CITRIC ACID MONOHYDRATE; SODIUM CHLORITE; ZINC GLUCONATE; AMMONIUM GLYCYRRHIZATE; ASCORBIC ACID; UBIDECARENONE; MENTHA ARVENSIS LEAF OIL; SPEARMINT OIL; WATER

TheraBreath®Plus Fresh Breath

Drug Facts

Active Ingredients

Sodium fluoride 0.24% (0.14% W/V fluoride ion)

Purpose

Anticavity Fluoride Dentifrice

Uses

Aids in the prevention of dental cavities

Warnings

Keep out of reach of children under 6 years of age.If more than used for brushing is accidentally swallowed, get medical help or contact a Poison Control Center right away.

Directions

Adults & Children 2 years of age and older: Brush teeth thoroughly, preferably after each meal or at least twice a day, or as directed by a dentist or doctor. Instruct children under 6 years of age in good brushing and rinsing habits (to minimize swallowing). Supervise children as necessary until capable of using without supervision. Children under 2 years of age: Consult a dentist or doctor.

Other information

- If spilled on fabrics, wash out immediately.
- This product was sealed with protective packaging at the laboratory.
- If seal is missing, do not use.

Inactive Ingredients

Sorbitol, Water (Aqua), Hydrated Silica, Glycerin (from vegetable sources), Xylitol, Natural Flavor, Cellulose Gum, Tetrapotassium Pyrophosphate, Tetrasodium Pyrophosphate, Sodium Benzoate, Aloe Barbadensis Leaf Juice, Citric Acid, Sodium Chlorite, Zinc Gluconate, Ammonium Glycyrrhizate, Ascorbic Acid (Vitamin C), Ubiquinone (COQ10), Mentha Arvensis (Cornmint) Leaf Oil, Mentha Viridis (Spearmint) Leaf Oil, Natural Fragrance (Parfum)

PRINCIPAL DISPLAY PANEL - 113.5 g Tube Label

ANTICAVITY TOOTHPASTE

CLINICAL FORMULA
TheraBreath®
PLUS

MAXIMUM STRENGTH

FRESH BREATH

TOOTHPASTE

FRESHENS BREATH FOR 24 HOURS*

Fortified with Zinc, Xylitol and Aloe
Nothing Works Faster and Lasts Longer
to Prevent Bad Breath

Dr. Harold Katz

net wt. 4 oz. • 113.5 g

PEPPERMINT